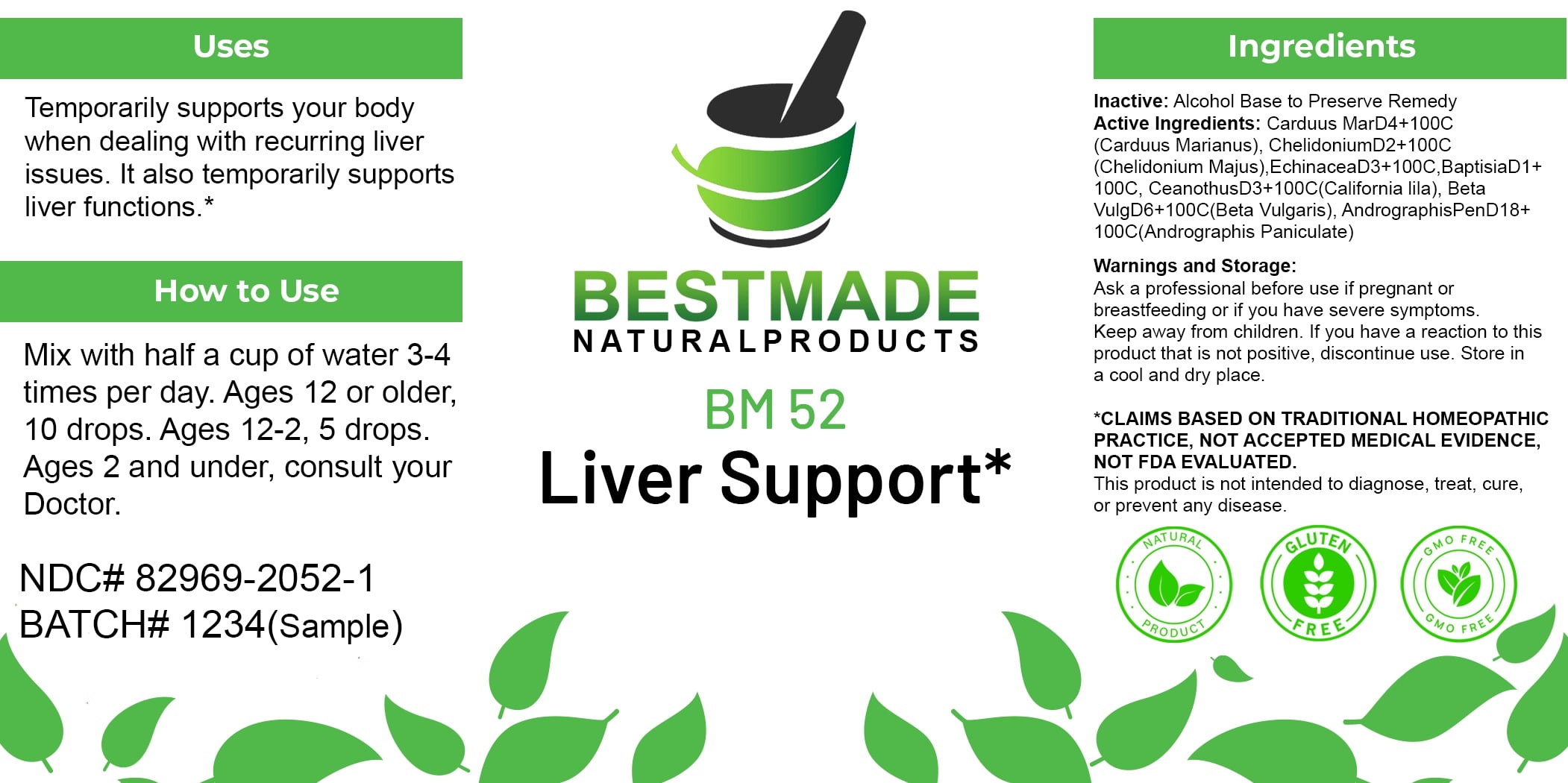 DRUG LABEL: Bestmade Natural Products BM52
NDC: 82969-2052 | Form: LIQUID
Manufacturer: Bestmade Natural Products
Category: homeopathic | Type: HUMAN OTC DRUG LABEL
Date: 20250123

ACTIVE INGREDIENTS: SILYBUM MARIANUM SEED 100 [hp_C]/100 [hp_C]; CHELIDONIUM MAJUS 100 [hp_C]/100 [hp_C]; BAPTISIA TINCTORIA ROOT 100 [hp_C]/100 [hp_C]; ECHINACEA, UNSPECIFIED 100 [hp_C]/100 [hp_C]; CEANOTHUS AMERICANUS LEAF 100 [hp_C]/100 [hp_C]; BETA VULGARIS 100 [hp_C]/100 [hp_C]; ANDROGRAPHIS PANICULATA WHOLE 100 [hp_C]/100 [hp_C]
INACTIVE INGREDIENTS: ALCOHOL 100 [hp_C]/100 [hp_C]

BM52

DOSAGE AND ADMINISTRATION

How to Use

Mix with half a cup of water 3-4 times per day. Ages 12 or older, 10 drops. Ages 12-2, 5 drops. Ages 2 and under, consult your Doctor.

Uses

Temporarily supports your body when dealing with recurring liver issues. It also temporarily supports liver functions.*

*CLAIMS BASED ON TRADITIONAL HOMEOPATHIC PRACTICE, NOT ACCEPTED MEDICAL EVIDENCE. NOT FDA EVALUATED.

This product is not intended to diagnose, treat, cure, or prevent any disease.

Uses

Temporarily supports your body when dealing with recurring liver issues. It also temporarily supports liver functions.*

*CLAIMS BASED ON TRADITIONAL HOMEOPATHIC PRACTICE, NOT ACCEPTED MEDICAL EVIDENCE. NOT FDA EVALUATED.

This product is not intended to diagnose, treat, cure, or prevent any disease.

ACTIVE INGREDIENT

Active Ingredients: Carduus Mar D4+100C (Carduus Marianus), Chelidonium D2+100C (Chelidonium Majus), Echinacea D3+100C, Baptisia D1+100C, Ceanothus D3+100C (California lila), Beta Vulg D6+100C (Beta Vulgaris), Andrographis Pen D18+100C (Andrographis Paniculate)

INACTIVE INGREDIENT

Ingredients

Inactive: Alcohol Base to Preserve Remedy

KEEP OUT OF REACH OF CHILDREN

Warnings and Storage:

Ask a professional before use if pregnant or breastfeeding or if you have severe symptoms. Keep away from children. If you have a reaction to this product that is not positive, discontinue use. Store in a cool and dry place.

Warnings and Storage:

Ask a professional before use if pregnant or breastfeeding or if you have severe symptoms. Keep away from children. If you have a reaction to this product that is not positive, discontinue use. Store in a cool and dry place.

*CLAIMS BASED ON TRADITIONAL HOMEOPATHIC PRACTICE, NOT ACCEPTED MEDICAL EVIDENCE. NOT FDA EVALUATED.

This product is not intended to diagnose, treat, cure, or prevent any disease.

Entire package label